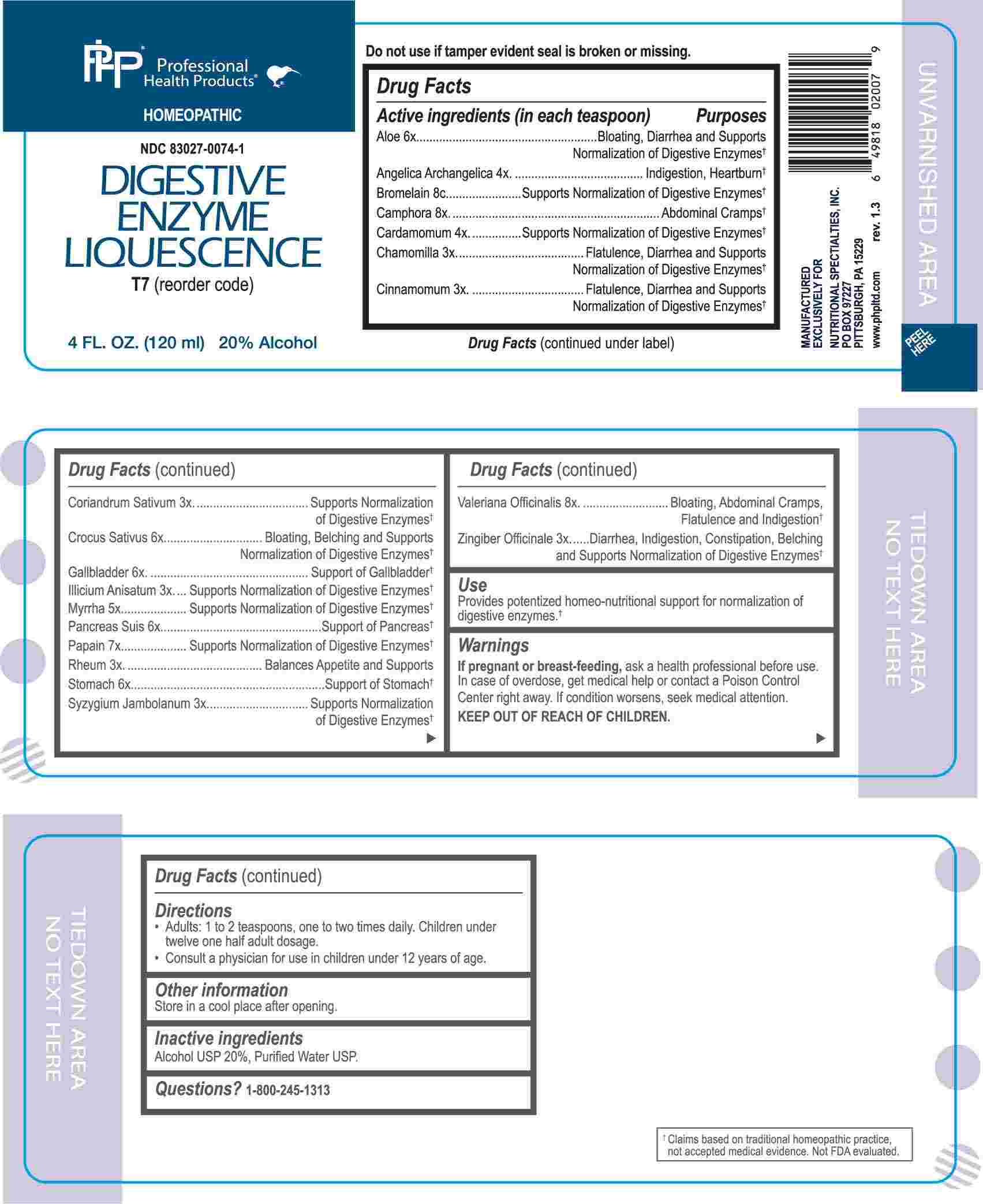 DRUG LABEL: Digestive Enzyme Liquescence
NDC: 83027-0074 | Form: LIQUID
Manufacturer: Nutritional Specialties, Inc.
Category: homeopathic | Type: HUMAN OTC DRUG LABEL
Date: 20240903

ACTIVE INGREDIENTS: MATRICARIA CHAMOMILLA WHOLE 3 [hp_X]/1 mL; CINNAMON 3 [hp_X]/1 mL; CORIANDER 3 [hp_X]/1 mL; STAR ANISE 3 [hp_X]/1 mL; RHEUM PALMATUM ROOT 3 [hp_X]/1 mL; SYZYGIUM CUMINI SEED 3 [hp_X]/1 mL; GINGER 3 [hp_X]/1 mL; ANGELICA ARCHANGELICA ROOT 4 [hp_X]/1 mL; ELETTARIA CARDAMOMUM WHOLE 4 [hp_X]/1 mL; MYRRH 5 [hp_X]/1 mL; ALOE 6 [hp_X]/1 mL; SAFFRON 6 [hp_X]/1 mL; BOS TAURUS GALLBLADDER 6 [hp_X]/1 mL; SUS SCROFA PANCREAS 6 [hp_X]/1 mL; SUS SCROFA STOMACH 6 [hp_X]/1 mL; PAPAIN 7 [hp_X]/1 mL; CAMPHOR (NATURAL) 8 [hp_X]/1 mL; VALERIAN 8 [hp_X]/1 mL; BROMELAINS 8 [hp_C]/1 mL
INACTIVE INGREDIENTS: WATER; ALCOHOL

DRUG FACTS:

ACTIVE INGREDIENTS:

(in each teaspoon) Aloe 6X, Angelica Archangelica 4X, Bromelain 8C, Camphora 8X, Cardamomum 4X, Chamomilla 3X, Cinnamomum 3X, Coriandrum Sativum 3X, Crocus Sativus 6X, Gallbladder 6X, Illicium Anisatum 3X, Myrrha 5X, Pancreas Suis 6X, Papain 7X, Rheum 3X, Stomach 6X, Syzygium Jambolanum 3X, Valeriana Officinalis 8X, Zingiber Officinale 3X.

PURPOSE:

Aloe – Bloating, Diarrhea and Supports Normalization of Digestive Enzymes,† Angelica Archangelica – Indigestion, Heartburn,† Bromelain – Supports Normalization of Digestive Enzymes,† Camphora – Abdominal Cramps,† Cardamomum – Supports Normalization of Digestive Enzymes,† Chamomilla – Flatulence, Diarrhea and Supports Normalization of Digestive Enzymes,† Cinnamomum – Flatulence, Diarrhea and Supports Normalization of Digestive Enzymes,† Coriandrum Sativum - Supports Normalization of Digestive Enzymes,† Crocus Sativus – Bloating, Belching and Supports Normalization of Digestive Enzymes,† Gallbladder – Support of Gallbladder,† Illicium Anisatum – Supports Normalization of Digestive Enzymes,† Myrrha - Supports Normalization of Digestive Enzymes,† Pancreas Suis – Support of Pancreas,† Papain – Supports Normalization of Digestive Enzymes,† Rheum – Balances Appetite and Supports,† Stomach – Support of Stomach,† Syzygium Jambolanum – Supports Normalization of Digestive Enzymes,† Valeriana Officinalis – Bloating, Abdominal Cramps, Flatulence and Indigestion,† Zingiber Officinale – Diarrhea, Indigestion, Constipation, Belching and Supports Normalization of Digestive Enzymes†

USES:

Provides potentized homeo-nutritional support for normalization of digestive enzymes.†

†Claims based on traditional homeopathic practice, not accepted medical evidence. Not FDA evaluated.

WARNINGS:

If pregnant or breast-feeding, ask a health professional before use.

In case of overdose, get medical help or contact a Poison Control Center right away.

If condition worsens, seek medical attention.

KEEP OUT OF REACH OF CHILDREN

Do not use if tamper evident seal is broken or missing.

Store in a cool place after opening

KEEP OUT OF REACH OF CHILDREN:

In case of overdose, get medical help or contact a Poison Control Center right away.

DIRECTIONS:

• Adults 1 to 2 teaspoons, one to two times daily. Children under twelve one half adult dosage.

• Consult a physician for use in children under 12 years of age.

INACTIVE INGREDIENTS:

Alcohol USP 20%, Purified Water USP.

QUESTIONS:

MANUFACTURED EXCLUSIVELY FOR

NUTRITIONAL SPECIALTIES, INC.

PO BOX 97227

PITTSBURG, PA 15229

www.phpltd.com

PACKAGE LABEL DISPLAY:

Professional

Health Products

HOMEOPATHIC

NDC 83027-0074-1

DIGESTIVE ENZYME

LIQUESCENCE

4 FL. OZ (120 ml)